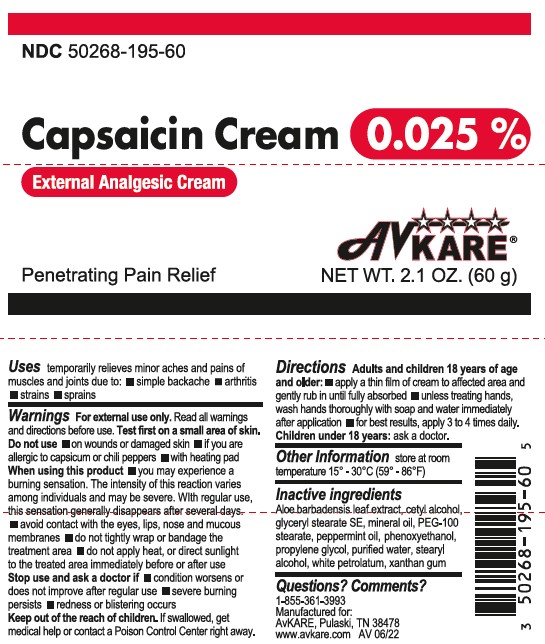 DRUG LABEL: Capsaicin
NDC: 50268-195 | Form: CREAM
Manufacturer: AvPAK
Category: otc | Type: HUMAN OTC DRUG LABEL
Date: 20260108

ACTIVE INGREDIENTS: CAPSAICIN 0.25 mg/1 g
INACTIVE INGREDIENTS: GLYCERYL STEARATE SE; CETYL ALCOHOL; PHENOXYETHANOL; GLYCERYL STEARATE/PEG-100 STEARATE; PETROLATUM; STEARYL ALCOHOL; XANTHAN GUM; PEPPERMINT OIL; ALOE VERA LEAF; MINERAL OIL; PROPYLENE GLYCOL; WATER

Capsaicin Cream 0,025%

Drug Facts

Active ingredient

Capsaicin 0.025%

Purpose

External analgesic

Uses

temporarily relieves minor aches and pains of muscles and joints due to:

- simple backache
- arthritis
- strains
- sprains

Warnings

For external use only

Read all warnings and directions before use. Test first on small area of skin.

Do not use

- on wounds or damaged skin
- if you are allergic to capsicum or chili peppers
- with heating pad

When using this product

- you may experience a burning sensation. The intensity of this reaction varies among individuals and may be severe. With regular use, this sensation generally disappears after several days.
- avoid contact with the eyes, lips, nose and mucous membranes
- do not tightly wrap or bandage the treated area
- do not apply heat to the treated area immediately before or after use

Stop use and ask a doctor if

- condition worsens or does not improve after regular use
- severe burning persists
- redness or blistering occurs

Keep out of reach of children. If swallowed, get medical help or contact a Poison Control Center immediately.

Directions

Adults and children 18 years of age and older:

- apply a thin film of cream to affected area and gently rub in until fully absorbed
- unless treating hands, wash hands thoroughly with soap and water immediately after application
- for best results, apply 3 to 4 times daily.

Children under 18 years: ask a doctor

Other information

store at room temperature 15° - 30°C (59° - 86°F)

Inactive ingredients

Aloe barbadensis leaf extract, cetyl alcohol, glyceryl stearate SE, mineral oil, PEG-100 stearate, peppermint oil, phenoxyethanol, propylene glycol, purified water, stearyl alcohol, white petrolatum, xanthan gum

Questions or comments?

1-855-361-3993

Manufactured for:
AvKARE, Pulaski, TN 38478

www.avkare.com

AV 06/22